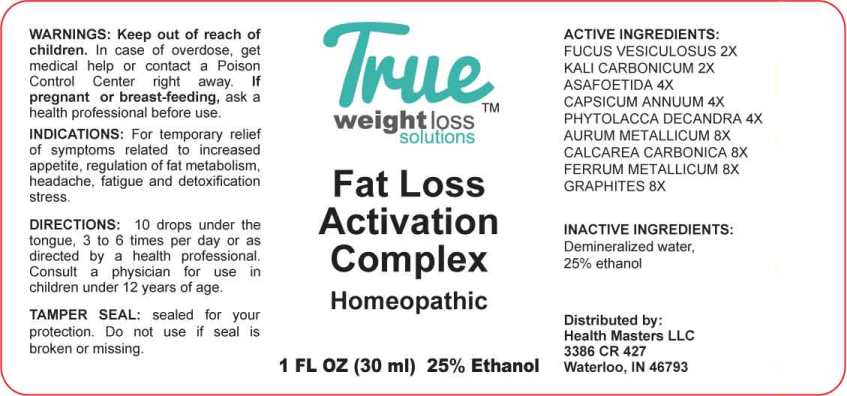 DRUG LABEL: Fat Loss Activation Complex
NDC: 73162-0004 | Form: LIQUID
Manufacturer: Health Masters LLC
Category: homeopathic | Type: HUMAN OTC DRUG LABEL
Date: 20230406

ACTIVE INGREDIENTS: FUCUS VESICULOSUS 2 [hp_X]/1 mL; POTASSIUM CARBONATE 2 [hp_X]/1 mL; FERULA ASSA-FOETIDA RESIN 4 [hp_X]/1 mL; CAPSICUM 4 [hp_X]/1 mL; PHYTOLACCA AMERICANA ROOT 4 [hp_X]/1 mL; GOLD 8 [hp_X]/1 mL; OYSTER SHELL CALCIUM CARBONATE, CRUDE 8 [hp_X]/1 mL; IRON 8 [hp_X]/1 mL; GRAPHITE 8 [hp_X]/1 mL
INACTIVE INGREDIENTS: WATER; ALCOHOL

DRUG FACTS:

ACTIVE INGREDIENTS:

Fucus Vesiculosus 2X, Kali Carbonicum 2X, Asafoetida 4X, Capsicum Annuum 4X, Phytolacca Decandra 4X, Aurum Metallicum 8X, Calcarea Carbonica 8X, Ferrum Metallicum 8X, Graphites 8X.

PURPOSE:

For temporary relief of symptoms related to increased appetite, regulation of fat metabolism, headache, fatigue and detoxification stress.

WARNINGS:

Keep out of reach of children. In case of overdose, get medical help or contact a Poison Control Center right away.

If pregnant or breast-feeding, ask a health professional before use.

TAMPER SEAL: Sealed for your protection. Do not use if seal is broken or missing.

KEEP OUT OF REACH OF CHILDREN:

In case of overdose, get medical help or contact a Poison Control Center right away.

DIRECTIONS:

10 drops under the tongue, 3 to 6 times per day or as directed by a health professional. Consult a physician for use in children under 12 years of age.

INDICATIONS:

For temporary relief of symptoms related to increased appetite, regulation of fat metabolism, headache, fatigue and detoxification stress.

INACTIVE INGREDIENTS:

Demineralized water, 25% ethanol

QUESTIONS:

Distributed by:

Health Masters LLC

3386 CR 427

Waterloo, IN 46793

PACKAGE LABEL DISPLAY:

True

weightloss ™
solutions

Fat Loss Activation

Complex

Homeopathic
1 FL OZ (30 ml)